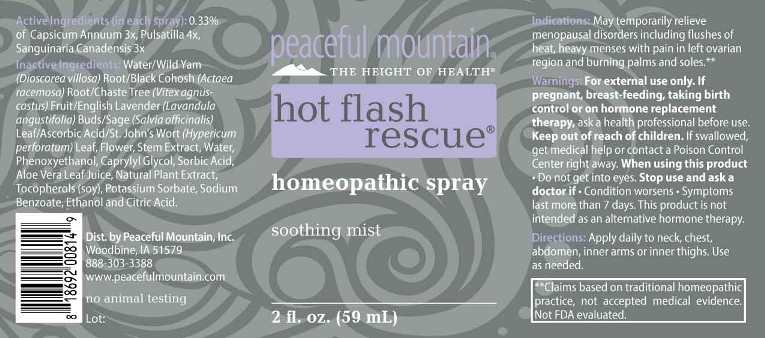 DRUG LABEL: Hot Flash Rescue
NDC: 43846-0081 | Form: SPRAY
Manufacturer: Peaceful Mountain, Inc.
Category: homeopathic | Type: HUMAN OTC DRUG LABEL
Date: 20240613

ACTIVE INGREDIENTS: CAPSICUM 3 [hp_X]/1 mL; PULSATILLA PRATENSIS WHOLE 4 [hp_X]/1 mL; SANGUINARIA CANADENSIS ROOT 3 [hp_X]/1 mL
INACTIVE INGREDIENTS: WATER; PHENOXYETHANOL; CAPRYLYL GLYCOL; SORBIC ACID; ALOE VERA LEAF; OREGANO; .ALPHA.-TOCOPHEROL; POTASSIUM SORBATE; DIOSCOREA VILLOSA TUBER; BLACK COHOSH; CHASTE TREE FRUIT; LAVANDULA ANGUSTIFOLIA FLOWER; SAGE; ASCORBIC ACID; HYPERICUM PERFORATUM; ALCOHOL; CITRIC ACID MONOHYDRATE

Drug Facts:

ACTIVE INGREDIENTS:

(in each spray): 0.33% of Capsicum Annuum 3X, Pulsatilla (Pratensis) 4X, Sanguinaria Canadensis 3X.

INDICATIONS:

May temporarily relieve menopausal disorders including flushes of heat, heavy menses with pain in left ovarian region and burning palms and soles. **

**Claims based on traditional homeopathic practice, not accepted medical evidence. Not FDA evaluated.

WARNINGS:

For external use only. If pregnant, breast-feeding, taking birth control or on hormone replacement therapy, ask a health professional before use.

Keep out of reach of children. If swallowed, get medical help or contact a Poison Control Center right away.

When using this product • Do not get into eyes.

Stop use and ask a doctor if Condition worsens - Symptoms last more than 7 days.

This product is not intended as an alternative hormone therapy.

Keep out of reach of children. If swallowed, get medical help or contact a Poison Control Center right away.

DIRECTIONS:

Apply daily to neck, chest, abdomen, inner arms or inner thighs. Use as needed.

INDICATIONS:

May temporarily relieve menopausal disorders including flushes of heat, heavy menses with pain in left ovarian region and burning palms and soles. **

**Claims based on traditional homeopathic practice, not accepted medical evidence. Not FDA evaluated.

INACTIVE INGREDIENTS:

Water, Wild Yam (Dioscorea Villosa) Root, Black Cohosh (Actaea Racemosa) Root, Chaste Tree (Vitex agnus-castus) Fruit, Lavender (Lavandula angustifolia) Buds, Sage (Salvia officinalis) Leaf, Ascorbic Acid, St John’s Wort (Hypericum Perforatum) Aerial Parts, Purified Water, Phenoxyethanol, Caprylyl Glycol, Sorbic Acid, Aloe Barbadensis Leaf Juice, Tocopherols (soy), Natural Plant Extract, Potassium Sorbate, Ethanol, Citric Acid.

QUESTIONS:

Dist. by Peaceful Mountain, Inc.

Woodbine, IA 51579

888-303-3388

www.peacefulmountain.com

no animal testing

PACKAGE LABEL DISPLAY:

peaceful mountain

THE HEIGHT OF HEALTH

hot flash rescue

homeopathic spray

soothing mist

2 fl. oz. (59 ml)